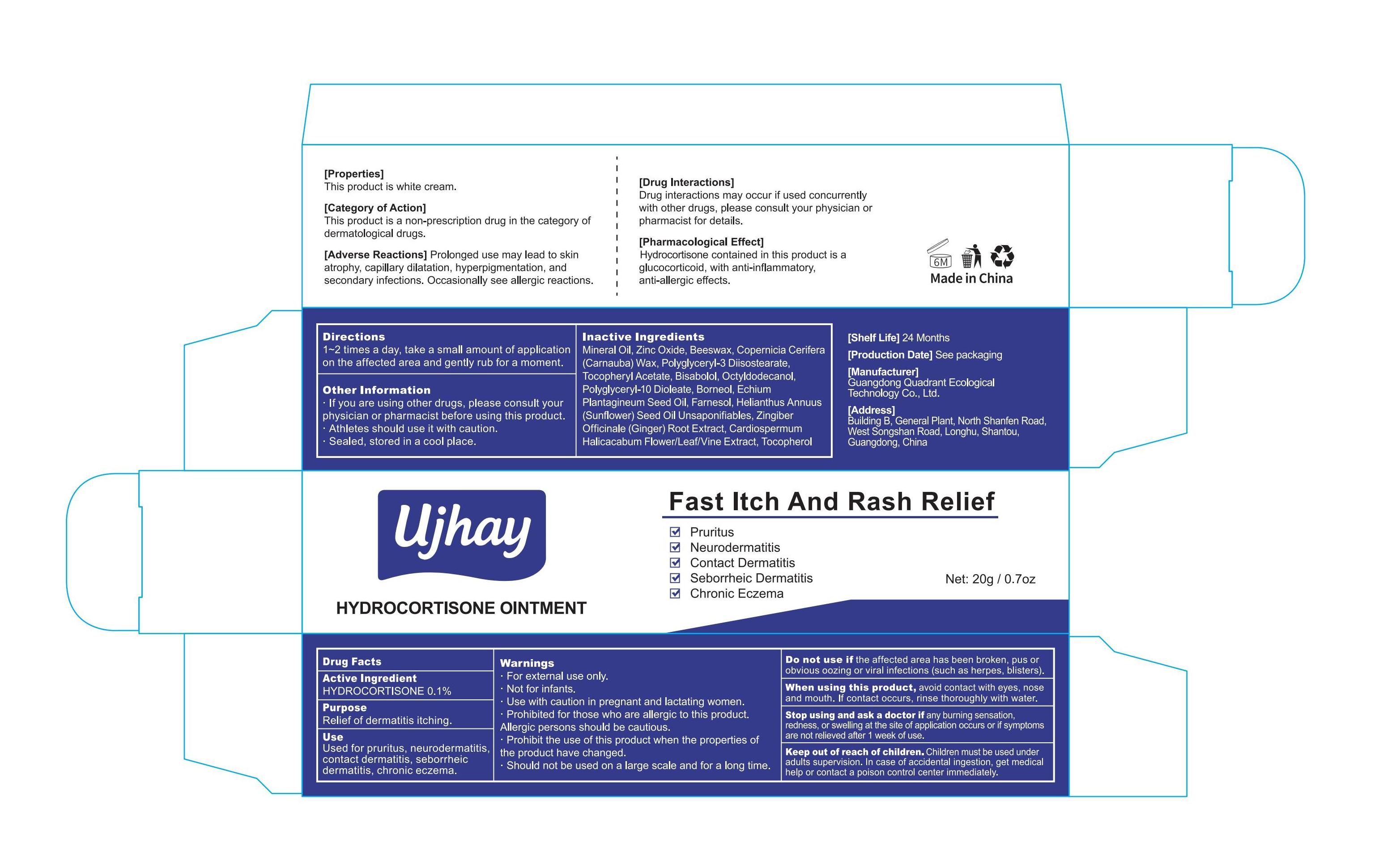 DRUG LABEL: Ujhay  Hydrocortisone Ointment.
NDC: 76986-010 | Form: OINTMENT
Manufacturer: Guangdong Quadrant Ecological Technology Co., Ltd.
Category: otc | Type: HUMAN OTC DRUG LABEL
Date: 20250727

ACTIVE INGREDIENTS: HYDROCORTISONE 0.1 g/100 g
INACTIVE INGREDIENTS: HELIANTHUS ANNUUS (SUNFLOWER) SEED OIL UNSAPONIFIABLES; FARNESOL; GINGER; ALPHA-TOCOPHEROL ACETATE; BISABOLOL; OCTYLDODECANOL; POLYGLYCERYL-10 DIOLEATE; CARDIOSPERMUM HALICACABUM FLOWERING TOP; ZINC OXIDE; ECHIUM LYCOPSIS FRUIT OIL; COPERNICIA CERIFERA (CARNAUBA) WAX; POLYGLYCERYL-3 DIISOSTEARATE; MINERAL OIL; BEESWAX; TOCOPHEROL

76986-010

Active Ingredient

HYDROCORTISONE 0.1%

Purpose

Relief of dermatitis itching.

Use

Used for pruritus, neurodermatitis, contact dermatitis, seborrheic dermatitis, chronic eczema.

Warnings

·For external use only.
·Not for infants.
·Use with caution in pregnant and lactating women.
·Prohibited for those who are allergic to this product. Allergic persons should be cautious.
·Prohibit the use of this product when the properties of the product have changed.
·Should not be used on a large scale and for a long time.

Do not use if the affected area has been broken, pus or obvious oozing or viral infections (such as herpes, blisters).

When Using

When using this product, avoid contact with eyes, nose and mouth. If contact occurs, rinse thoroughly with water.

Stop Use

Stop using and ask a doctor if any burning sensation, redness, or swelling at the site of application occurs or if symptoms are not relieved after 1 week of use.

Ask Doctor

In case of accidental ingestion, get medical help or contact a poison control center immediately.

Keep out of reach of children. Children must be used under adults supervision.

Directions

1~2 times a day, take a small amount of application on the affected area and gently rub for a moment.

Other information

·If you are using other drugs, please consult your physician or pharmacist before using this product.
·Athletes should use it with caution.
·Sealed, stored in a cool place.

Inactive ingredients

MINERAL OIL,ZINC OXIDE,BEESWAX,COPERNICIA CERIFERA (CARNAUBA) WAX,POLYGLYCERYL-3 DIISOSTEARATE,TOCOPHERYL ACETATE,BISABOLOL,OCTYLDODECANOL,POLYGLYCERYL-10 DIOLEATE,BORNEOL,ECHIUM PLANTAGINEUM SEED OIL,FARNESOL,HELIANTHUS ANNUUS (SUNFLOWER) SEED OIL UNSAPONIFIABLES,ZINGIBER OFFICINALE (GINGER) ROOT EXTRACT,CARDIOSPERMUM HALICACABUM FLOWER/LEAF/VINE EXTRACT,TOCOPHEROL